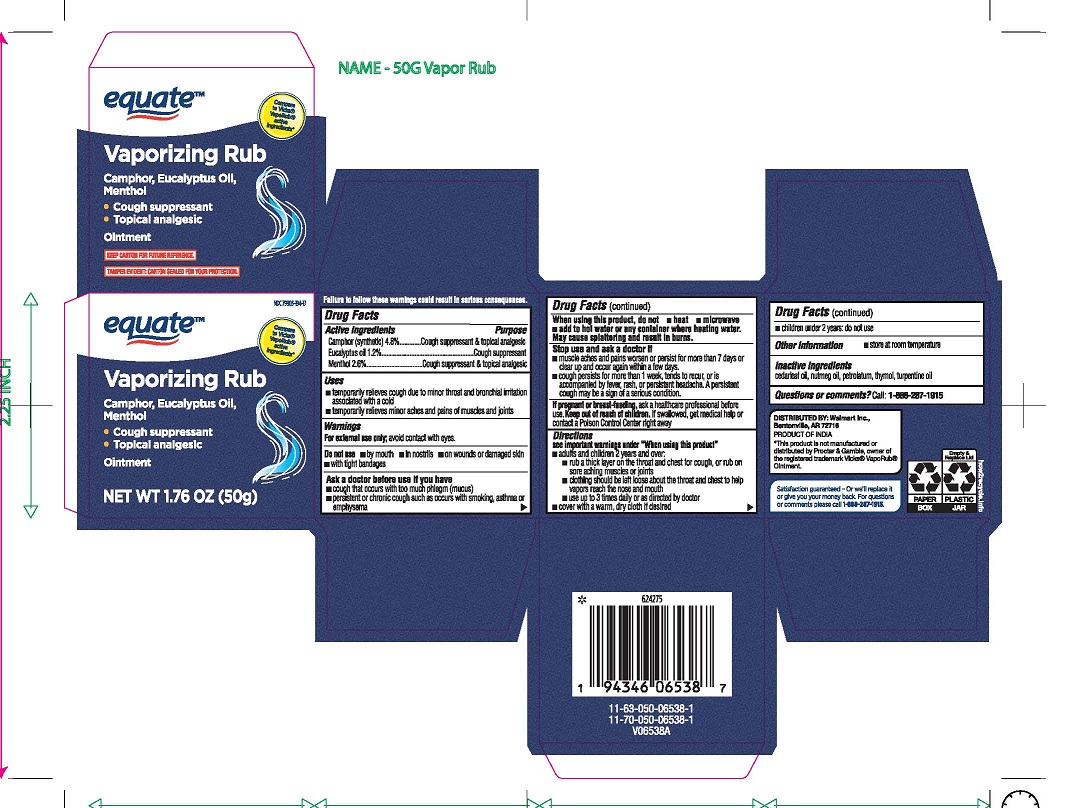 DRUG LABEL: Equate
NDC: 79903-194 | Form: OINTMENT
Manufacturer: Walmart Inc
Category: otc | Type: HUMAN OTC DRUG LABEL
Date: 20251008

ACTIVE INGREDIENTS: MENTHOL 2.6 g/100 g; CAMPHOR (SYNTHETIC) 4.8 g/100 g; EUCALYPTUS OIL 1.2 g/100 g
INACTIVE INGREDIENTS: TURPENTINE OIL; CEDAR LEAF OIL; NUTMEG OIL; PETROLATUM; THYMOL

Equate Vaporizing Rub

Active ingredients

Camphor (synthetic) 4.8% .....................................................Cough suppressant & topical analgesic

Eucalyptus Oil 1.2% .............................................................. Cough suppressant

Menthol 2.6% .........................................................................Cough suppressant & topical analgesic

Purpose

Cough suppressant & topical analgesic

Uses

- temporarily relieves cough due to minor throat and bronchial irritation associated with a cold
- temporarily relieves minor aches and pains of muscles and joints

Warnings

For external use only; avoid contact with eyes. Do not use

- by mouth
- in nostrils
- on wounds or damaged skin
- with tight bandages

Ask a doctor before use if you have

- cough that occurs with too much phlegm (mucus)
- persistent or chronic cough such as occurs with smoking, asthma or emphysema

When using this product, do not

- heat
- microwave
- add to hot water or any container where heating water.

May cause splattering and result in burns.

Stop use and ask a doctor if

- muscle aches and pains worsen or persist for more than 7 days or clear up and occur again within a few days.
- cough persists for more than 1 week, tends to recur, or is accompanied by fever, rash, or persistent headache. A persistent cough may be a sign of a serious condition.

If pregnant or breast-feeding,

ask a health professional before use.

Keep out of reach of children.

If swallowed, get medical help or contact a Poison Control Center right away.

Directions

See important warnings under "When using this product"

• adults and children 2 years and over:

> Rub a thick layer on the throat and chest for cough, or rub on sore aching muscles or joints

> Clothing should be left loose about the throat and chest to help vapors reach the nose and mouth
> Use up to 3 times daily or as directed by doctor
Cover with a warm, dry cloth if desired

• children under 2 years: do not use

Other information

store at room temperature

Inactive ingredients

cedarleaf oil, nutmeg oil, petrolatum, thymol, turpentine oil